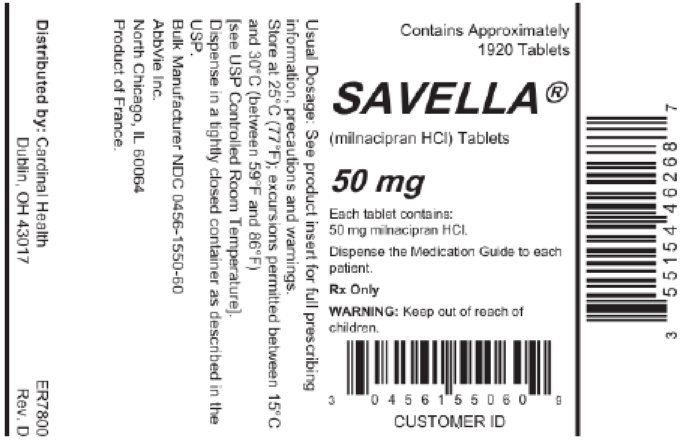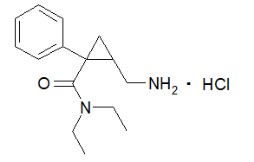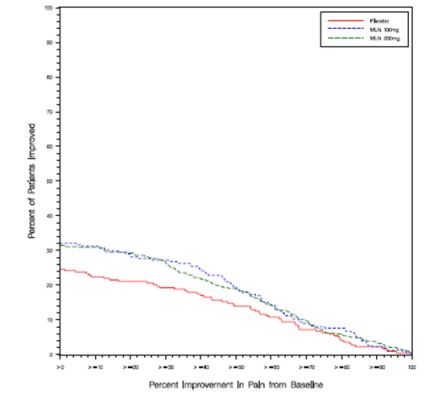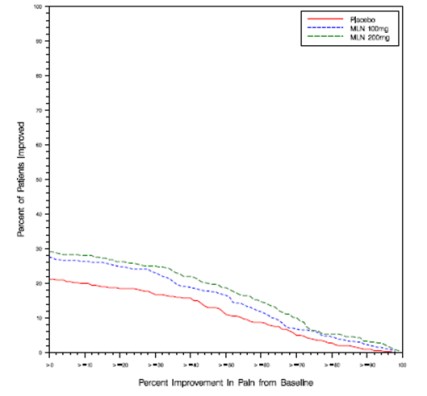 DRUG LABEL: Savella
NDC: 55154-4626 | Form: TABLET, FILM COATED
Manufacturer: Cardinal Health 107, LLC
Category: prescription | Type: HUMAN PRESCRIPTION DRUG LABEL
Date: 20260126

ACTIVE INGREDIENTS: MILNACIPRAN HYDROCHLORIDE 50 mg/1 1
INACTIVE INGREDIENTS: DIBASIC CALCIUM PHOSPHATE DIHYDRATE; POVIDONE, UNSPECIFIED; CARBOXYMETHYLCELLULOSE CALCIUM; SILICON DIOXIDE; MAGNESIUM STEARATE; TALC; POLYVINYL ALCOHOL, UNSPECIFIED; POLYETHYLENE GLYCOL, UNSPECIFIED; TITANIUM DIOXIDE

HIGHLIGHTS OF PRESCRIBING INFORMATION

These highlights do not include all the information needed to use SAVELLA safely and effectively. See full prescribing information for SAVELLA.
SAVELLA® (milnacipran HCl) tablets
Initial U.S. Approval: 2009

WARNING: SUICIDALITY AND ANTIDEPRESSANT DRUGS

See full prescribing information for complete boxed warning.

- Increased risk of suicidal ideation, thinking, and behavior in children, adolescents, and young adults taking antidepressants for major depressive disorder (MDD) and other psychiatric disorders (5.1).
- SAVELLA is not approved for use in pediatric patients (1, 8.4).

1 INDICATIONS AND USAGE

- SAVELLA® is a selective serotonin and norepinephrine reuptake inhibitor (SNRI) indicated for the management of fibromyalgia (1).
- SAVELLA is not approved for use in pediatric patients (1).

2 DOSAGE AND ADMINISTRATION

- Administer SAVELLA in two divided doses per day (2.1).
- Based on efficacy and tolerability, dosing may be titrated according to the following schedule (2.1):
Day 1: 12.5 mg once
Days 2-3: 25 mg/day (12.5 mg twice daily)
Days 4-7: 50 mg/day (25 mg twice daily)
After Day 7: 100 mg/day (50 mg twice daily)
- Recommended dose is 100 mg/day (2.1).
- May be increased to 200 mg/day based on individual patient response (2.1).
- Adjust dose in patients with severe renal impairment (2.2).

3 DOSAGE FORMS AND STRENGTHS

- Tablets: 12.5 mg, 25 mg, 50 mg, 100 mg (3)

4 CONTRAINDICATIONS

- Serotonin Syndrome and MAOIs: Do not use MAOIs intended to treat psychiatric disorders with SAVELLA or within 5 days of stopping treatment with SAVELLA. Do not use SAVELLA within 14 days of stopping an MAOI intended to treat psychiatric disorders. In addition, do not start SAVELLA in a patient who is being treated with linezolid or intravenous methylene blue (4.1, 5.2).

5 WARNINGS AND PRECAUTIONS

- Suicidality: Monitor for worsening of depressive symptoms and suicide risk (5.1).
- Serotonin Syndrome: Increased risk when co-administered with other serotonergic agents, but also when taken alone. If it occurs, discontinue SAVELLA and any other serotonergic agents, and initiate supportive treatment (5.2).
- Elevated Blood Pressure and Heart Rate: SAVELLA may increase blood pressure and heart rate. Measure blood pressure and heart rate prior to initiating treatment with SAVELLA and monitor periodically throughout treatment (5.3, 5.4).
- Seizures: Cases have been reported with SAVELLA therapy. Prescribe SAVELLA with care in patients with a history of seizure disorder (5.5).
- Hepatotoxicity: SAVELLA may cause elevations of ALT and AST. Avoid concomitant use of SAVELLA in patients with substantial alcohol use or chronic liver disease (5.6).
- Discontinuation: Withdrawal symptoms have been reported in patients when discontinuing treatment with SAVELLA. A gradual dose reduction is recommended (5.7).
- Increased Risk of Bleeding: SAVELLA may increase the risk of bleeding events. Caution patients about the risk of bleeding associated with the concomitant use of SAVELLA and NSAIDs, aspirin, or other drugs that affect coagulation (5.9).
- History of Dysuria: Male patients with a history of obstructive uropathies may experience higher rates of genitourinary adverse events (5.11).
- Sexual Dysfunction: SAVELLA use may cause symptoms of sexual dysfunction (5.12).

6 ADVERSE REACTIONS

The most frequently occurring adverse reactions (≥ 5% and greater than placebo) were nausea, headache, constipation, dizziness, insomnia, hot flush, hyperhidrosis, vomiting, palpitations, heart rate increased, dry mouth, and hypertension (6.1).

To report SUSPECTED ADVERSE REACTIONS, contact AbbVie at 1-800-678-1605 or FDA at 1-800-FDA-1088 or www.fda.gov/medwatch.

7 DRUG INTERACTIONS

- SAVELLA is unlikely to be involved in clinically significant pharmacokinetic drug interactions (7).
- Pharmacodynamic interactions of SAVELLA with other drugs can occur (7).

8 USE IN SPECIFIC POPULATIONS

- Pregnancy: Third trimester use may increase risk for symptoms of poor adaptation (respiratory distress, temperature instability, feeding difficulty, hypotonia, tremor, irritability) in the neonate (8.1).

FULL PRESCRIBING INFORMATION

WARNING: SUICIDALITY AND ANTIDEPRESSANT DRUGS

SAVELLA is a selective serotonin and norepinephrine reuptake inhibitor (SNRI), similar to some drugs used for the treatment of depression and other psychiatric disorders. Antidepressants increased the risk compared to placebo of suicidal thinking and behavior (suicidality) in children, adolescents, and young adults in short-term studies of major depressive disorder (MDD) and other psychiatric disorders. Anyone considering the use of such drugs in a child, adolescent, or young adult must balance this risk with the clinical need. Short-term studies did not show an increase in the risk of suicidality with antidepressants compared to placebo in adults beyond age 24; there was a reduction in risk with antidepressants compared to placebo in adults aged 65 and older. Depression and certain other psychiatric disorders are themselves associated with increases in the risk of suicide. Patients of all ages who are started on SAVELLA should be monitored appropriately and observed closely for clinical worsening, suicidality, or unusual changes in behavior. Families and caregivers should be advised of the need for close observation and communication with the prescriber. SAVELLA is not approved for use in the treatment of major depressive disorder. SAVELLA is not approved for use in pediatric patients [see Indications and Usage (1), Warnings and Precautions (5.1), Use in Specific Populations (8.4)].

1 INDICATIONS AND USAGE

SAVELLA is indicated for the management of fibromyalgia.

SAVELLA is not approved for use in pediatric patients [see Use in Specific Populations (8.4)].

2 DOSAGE AND ADMINISTRATION

SAVELLA is given orally with or without food.

Taking SAVELLA with food may improve the tolerability of the drug.

2.1 Recommended Dosing

The recommended dose of SAVELLA is 100 mg/day (50 mg twice daily).

Based on efficacy and tolerability dosing may be titrated according to the following schedule:

Day 1: 12.5 mg once

Days 2-3: 25 mg/day (12.5 mg twice daily)

Days 4-7: 50 mg/day (25 mg twice daily)

After Day 7: 100 mg/day (50 mg twice daily)

Based on individual patient response, the dose may be increased to 200 mg/day (100 mg twice daily).

Doses above 200 mg/day have not been studied.

Taper SAVELLA and do not abruptly discontinue after extended use [see Dosage and Administration (2.4), Warnings and Precautions (5.7)].

2.2 Patients with Renal Insufficiency

No dosage adjustment is necessary in patients with mild renal impairment.

Use SAVELLA with caution in patients with moderate renal impairment.

For patients with severe renal impairment (indicated by an estimated creatinine clearance of 5-29 mL/min), reduce the maintenance dose by 50% to 50 mg/day (25 mg twice daily).

Based on individual patient response, the dose may be increased to 100 mg/day (50 mg twice daily).

SAVELLA is not recommended for patients with end-stage renal disease.

2.3 Patients with Hepatic Insufficiency

No dosage adjustment is necessary for patients with hepatic impairment.

As with any drug, exercise caution in patients with severe hepatic impairment.

2.4 Discontinuing SAVELLA

Withdrawal symptoms have been observed in clinical trials following discontinuation of milnacipran, as with other serotonin and norepinephrine re-uptake inhibitors (SNRIs) and selective serotonin re-uptake inhibitors (SSRIs). Monitor patients for these symptoms when discontinuing treatment. Taper SAVELLA and do not abruptly discontinue after extended use [see Warnings and Precautions (5.7)].

2.5 Switching a Patient to or from a Monoamine Oxidase Inhibitor (MAOI) Intended to Treat Psychiatric Disorders

At least 14 days should elapse between discontinuation of a MAOI intended to treat psychiatric disorders and initiation of therapy with SAVELLA. Conversely, allow at least 5 days after stopping SAVELLA before starting a MAOI intended to treat psychiatric disorders [see Contraindications (4.1)].

2.6 Use of SAVELLA with other MAOIs such as Linezolid or Methylene Blue

Do not start SAVELLA in a patient being treated with linezolid or intravenous methylene blue because there is increased risk of serotonin syndrome. In a patient who requires more urgent treatment of a psychiatric condition, consider other interventions, including hospitalization [see Contraindications (4.1)].

In some cases, a patient already receiving SAVELLA therapy may require urgent treatment with linezolid or intravenous methylene blue. If acceptable alternatives to linezolid or intravenous methylene blue treatment are not available and the potential benefits of linezolid or intravenous methylene blue treatment are judged to outweigh the risks of serotonin syndrome in a particular patient, discontinue SAVELLA promptly, and consider administering linezolid or intravenous methylene blue. Monitor the patient for symptoms of serotonin syndrome for 5 days or until 24 hours after the last dose of linezolid or intravenous methylene blue, whichever comes first. Therapy with SAVELLA may be resumed 24 hours after the last dose of linezolid or intravenous methylene blue [see Warnings and Precautions (5.2)].

The risk of administering methylene blue by non-intravenous routes (such as oral tablets or by local injection) or in intravenous doses much lower than 1 mg/kg with SAVELLA is unclear. The clinician should nevertheless be aware of the possibility of emergent symptoms of serotonin syndrome with such use [see Warnings and Precautions (5.2)].

3 DOSAGE FORMS AND STRENGTHS

Film-coated, immediate-release tablets in four strengths: 12.5 mg, 25 mg, 50 mg, and 100 mg of milnacipran hydrochloride.

12.5 mg tablets are round, blue, "F" on one side, "L" on the reverse side;

25 mg tablets are round, white, "FL" on one side, "25" on the reverse side;

50 mg tablets are oval, white, "FL" on one side, "50" on the reverse side;

100 mg tablets are oval, pink, "FL" on one side, "100" on the reverse side.

4 CONTRAINDICATIONS

4.1 Monoamine Oxidase Inhibitors (MAOIs)

The use of MAOIs intended to treat psychiatric disorders with SAVELLA or within 5 days of stopping treatment with SAVELLA is contraindicated because of an increased risk of serotonin syndrome. The use of SAVELLA within 14 days of stopping an MAOI intended to treat psychiatric disorders is also contraindicated [see Dosage and Administration (2.5), Warnings and Precautions (5.2)].

Starting SAVELLA in a patient who is being treated with MAOIs such as linezolid or intravenous methylene blue is also contraindicated because of an increased risk of serotonin syndrome [see Dosage and Administration (2.6), Warnings and Precautions (5.2)].

5 WARNINGS AND PRECAUTIONS

5.1 Suicide Risk

SAVELLA is a selective serotonin and norepinephrine re-uptake inhibitor (SNRI), similar to some drugs used for the treatment of depression and other psychiatric disorders.

Patients, both adult and pediatric, with depression or other psychiatric disorders may experience worsening of their depression and/or the emergence of suicidal ideation and behavior (suicidality) or unusual changes in behavior, whether or not they are taking these medications, and this risk may persist until significant remission occurs. Suicide is a known risk of depression and certain other psychiatric disorders, and these disorders themselves are the strongest predictors of suicide. There has been a long-standing concern, however, that antidepressants, including drugs that inhibit the reuptake of norepinephrine and/or serotonin, may have a role in inducing worsening of depression and the emergence of suicidality in certain patients during the early phases of treatment.

In the placebo-controlled clinical trials of adults with fibromyalgia, among the patients who had a history of depression at treatment initiation, the incidence of suicidal ideation was 0.5% in patients treated with placebo, 0% in patients treated with SAVELLA 100 mg/day, and 1.3% in patients treated with SAVELLA 200 mg/day. No suicides occurred in the short-term or longer-term (up to 1 year) fibromyalgia trials.

Pooled analyses of short-term placebo-controlled trials of drugs used to treat depression (SSRIs and others) showed that these drugs increase the risk of suicidal thinking and behavior (suicidality) in children, adolescents, and young adults (ages 18-24) with major depressive disorder (MDD) and other psychiatric disorders. Short-term studies did not show an increase in the risk of suicidality with these drugs compared to placebo in adults beyond age 24; there was a reduction in suicidality risk with antidepressants compared to placebo in adults age 65 and older.

The pooled analyses of placebo-controlled trials in children and adolescents with MDD, obsessive compulsive disorder (OCD), or other psychiatric disorders included a total of 24 short-term trials of 9 drugs used to treat depression in over 4400 patients. The pooled analyses of placebo-controlled trials in adults with MDD or other psychiatric disorders included a total of 295 short-term trials (median duration of 2 months) of 11 antidepressant drugs in over 77,000 patients.

There was considerable variation in risk of suicidality among drugs, but a tendency toward an increase in the younger patients for almost all drugs studied. There were differences in absolute risk of suicidality across the different indications, with the highest incidence in MDD. The risk of differences (drug versus placebo), however, were relatively stable within age strata and across indications. These risk differences (drug-placebo difference in the number of cases of suicidality per 1000 patients treated) are provided in Table 1.

Table 1: Risk Differences (Drug – Placebo) in the number of Cases of Suicidality, per 1000 patients treated
Age Range | Drug-Placebo Difference in Number of Cases of Suicidality per 1000 Patients Treated
< 18 | 14 additional cases
18-24 | 5 additional cases
 | Decreases Compared to Placebo
25-64 | 1 fewer case
≥ 65 | 6 fewer cases

No suicides occurred in any of the pediatric trials. There were suicides in the adult trials, but the number was not sufficient to reach any conclusion about drug effect on suicide.

It is unknown whether the suicidality risk extends to longer-term use, i.e., beyond several months.

However, there is substantial evidence from placebo-controlled maintenance trials in adults with depression that the use of antidepressants can delay the recurrence of depression.

All patients being treated with drugs inhibiting the reuptake of norepinephrine and/or serotonin for any indication should be monitored appropriately and observed closely for clinical worsening, suicidality, and unusual changes in behavior, especially during the initial few months of a course of drug therapy, or at times of dose changes, either increases or decreases.

The following symptoms, anxiety, agitation, panic attacks, insomnia, irritability, hostility, aggressiveness, impulsivity, akathisia (psychomotor restlessness), hypomania, mania, have been reported in adult and pediatric patients being treated with drugs inhibiting the reuptake of norepinephrine and/or serotonin for major depressive disorder as well as for other indications, both psychiatric and non-psychiatric. Although a causal link between the emergence of such symptoms and either the worsening of depression and/or the emergence of suicidal impulses has not been established, there is concern that such symptoms may represent precursors to emerging suicidality.

Consideration should be given to changing the therapeutic regimen, including possibly discontinuing the medication, in patients who may experience worsening depressive symptoms, or who are experiencing emergent suicidality or symptoms that might be precursors to worsening depression or suicidality, especially if these symptoms are severe or abrupt in onset, or were not part of the patient’s presenting symptoms.

If the decision has been made to discontinue treatment due to worsening depressive symptoms or emergent suicidality, medication should be tapered, as rapidly as is feasible, but with recognition that abrupt discontinuation can produce withdrawal symptoms [see Dosage and Administration (2.1, 2.4), Warnings and Precautions (5.7)].

Families and caregivers of patients being treated with drugs inhibiting the reuptake of norepinephrine and/or serotonin for major depressive disorder or other indications, both psychiatric and nonpsychiatric, should be alerted about the need to monitor patients for the emergence of agitation, irritability, unusual changes in behavior, and the other symptoms described above, as well as the emergence of suicidality, and to report such symptoms immediately to health care providers. Such monitoring should include daily observation by families and caregivers. Prescriptions for SAVELLA should be written for the smallest quantity of tablets consistent with good patient management, in order to reduce the risk of overdose.

5.2 Serotonin Syndrome

Selective-serotonin reuptake inhibitors (SSRIs) and serotonin-norepinephrine reuptake inhibitors (SNRIs), including SAVELLA, can precipitate serotonin syndrome, a potentially life-threatening condition. The risk is increased with concomitant use of other serotonergic drugs (including triptans, tricyclic antidepressants, fentanyl, tramadol, meperidine, methadone, lithium, tryptophan, buspirone, amphetamines, and St. John’s Wort) and with drugs that impair metabolism of serotonin i.e., MAOIs [see Contraindications (4), Drug Interactions (7)]. Serotonin syndrome can also occur when these drugs are used alone.

Serotonin syndrome symptoms may include mental status changes (e.g., agitation, hallucinations, delirium, and coma), autonomic instability (e.g., tachycardia, labile blood pressure, dizziness, diaphoresis, flushing, hyperthermia), neuromuscular symptoms (e.g., tremor, rigidity, myoclonus, hyperreflexia, incoordination), seizures, and/or gastrointestinal symptoms (e.g., nausea, vomiting, diarrhea).

The concomitant use of SAVELLA with MAOIs is contraindicated. In addition, do not initiate SAVELLA in a patient who is being treated with MAOIs such as linezolid or intravenous methylene blue. No reports involved the administration of methylene blue by other routes (such as oral tablets or local tissue injection). If it is necessary to initiate treatment with an MAOI such as linezolid or intravenous methylene blue in a patient taking SAVELLA, discontinue SAVELLA before initiating treatment with the MAOI [see Contraindications (4.1), Dosage and Administration (2.5, 2.6), Drug Interactions (7.1)].

Monitor all patients taking SAVELLA for the emergence of serotonin syndrome. Discontinue treatment with SAVELLA and any concomitant serotonergic agents immediately if the above events occur and initiate supportive symptomatic treatment. If concomitant use of SAVELLA with other serotonergic drugs is clinically warranted, inform patients of the increased risk for serotonin syndrome and monitor for symptoms.

5.3 Elevated Blood Pressure

A double-blind, placebo-controlled ambulatory blood pressure monitoring (ABPM) study was conducted to evaluate the effects of milnacipran (up to 200 mg/day) on blood pressure in 321 fibromyalgia patients. Among fibromyalgia patients who were normotensive at baseline, an analysis of the blood pressure findings demonstrated a substantially higher proportion of SAVELLA-treated patients had a hypertensive blood pressure measurement at the Week 4, 50 mg BID steady state visit (17.7% [n=21/119]) and the Week 7, 100 mg BID steady state visit (14.3% [n=15/105]) as compared to placebo-treated patients (3.7% [n=2/54] and 0% [0/49] at the Week 4 and Week 7 visits, respectively). Hypertension was defined as mean systolic blood pressure (SBP) ≥140 mmHg and change from baseline in mean SBP ≥10 mmHg or mean diastolic blood pressure (DBP) ≥90 mmHg and change from baseline in mean DBP ≥5 mmHg for the 12-hour period post AM study drug measurement at that visit. Furthermore, 1.9% (4/210) of SAVELLA-treated and 0.9% (1/111) of placebo patients discontinued treatment for increases in blood pressure.

The increased risk of blood pressure measurements in the hypertensive range in SAVELLA-treated patients is supported by substantial increases in mean SBP and DBP measurements observed in the ABPM study. Table 2 shows that, following treatment with SAVELLA 50 mg BID for three weeks in patients who were normotensive at baseline, the mean increase from baseline was 5 mmHg in systolic blood pressure (SBP) and diastolic blood pressure (DBP). After further treatment with SAVELLA 100 mg BID for two weeks, the mean increase from baseline in SBP and DBP was 6 mmHg. Similar elevations occurred in SAVELLA-treated patients who were hypertensive at baseline.

Table 2: Mean (Standard Error) Change from Baseline in Mean 24-hour Systolic and Diastolic Blood Pressure (mmHg) of Milnacipran or Placebo following 4 Weeks of Treatment (50mg BID) and a Subsequent 2 Weeks of Treatment (100mg BID)
 | Normotensive |  |  | Hypertensive
 | n | Systolic | Diastolic | n | Systolic | Diastolic
Placebo | 39 | 0(2) | -1(1) | 50 | 0(2) | 0(2)
50 mg BID* | 92 | 5(1) | 5(1) | 84 | 5(2) | 4(1)
Placebo | 37 | 0(2) | -1(1) | 47 | -1(2) | 0(1)
100 mg BID^ | 82 | 6(1) | 6(1) | 80 | 5(2) | 4(1)

*Blood pressure measurements made after 3 weeks of milnacipran 50mg BID

^Blood pressure measurements made after 2 weeks of milnacipran 100mg BID

Similar patterns of treatment-emergent blood pressure elevations were observed in Phase 3 and clinical pharmacology studies as manifested by an increased risk of new onset hypertension or substantial increases in end of study blood pressure measurements in patients with hypertension at baseline (Table 3).

Table 3: Blood pressure changes in Phase 3 randomized controlled trials
 | Milnacipran 50 mg BID | Milnacipran 100 mg BID | Placebo
FM patients normotensive at baseline who became hypertensive (defined as SBP ≥ 140 mmHg or DBP ≥ 90 mmHg on three consecutive post-baseline visits) | 20% | 17% | 7%
FM patients with sustained increases in SBP (increase of ≥ 15 mmHg on three consecutive post-baseline visits) | 9% | 6% | 2%
FM patients with sustained increases in DBP (increase of ≥ 10 mmHg on three consecutive post-baseline visits) | 13% | 10 % | 4%
FM patients hypertensive at baseline who had increases in SBP ≥ 15 mmHg at end of study | 10% | 7% | 4%
FM patients hypertensive at baseline who had increases in DBP ≥ 10 mmHg at end of study | 8% | 6% | 3%

Sustained increases in blood pressure may have adverse consequences. Cases of elevated blood pressure requiring immediate treatment have been reported.

Concomitant use of SAVELLA with drugs that increase blood pressure and heart rate has not been evaluated and such combinations should be used with caution [see Drug Interactions (7)].

Effects of SAVELLA on blood pressure in patients with significant hypertension or cardiac disease have not been systematically evaluated. SAVELLA should be used with caution in these patients.

Measure blood pressure prior to initiating treatment and periodically monitor blood pressure throughout SAVELLA treatment. Treat pre-existing hypertension and other cardiovascular disease before starting therapy with SAVELLA. For patients who experience a sustained increase in blood pressure while receiving SAVELLA, either reduce the dose or discontinue treatment with SAVELLA if clinically warranted.

5.4 Elevated Heart Rate

A double-blind, placebo-controlled ABPM study was conducted to evaluate the effects of milnacipran (up to 200 mg/day) on blood pressure in 321 fibromyalgia patients [see Warnings and Precautions (5.3)]. Information on heart rate was also collected. Following treatment with SAVELLA 50mg BID for three weeks in patients who were normotensive at baseline, the mean increase in mean 24-hour heart rate from baseline was 13 beats per minute. After further treatment with SAVELLA 100 mg BID for two weeks, the mean increase from baseline in heart rate was 13 beats per minute.

Similar trends were observed in the clinical trials where SAVELLA treatment was associated with mean increases in heart rate of approximately 7 to 8 beats per minute [see Adverse Reactions (6.1)].

Increases in heart rate ≥ 20 beats per minute occurred more frequently in SAVELLA-treated patients when compared to placebo (8% in the SAVELLA 50 mg BID and 100 mg BID treatment arms versus 0.3% in the placebo arm).

SAVELLA has not been systematically evaluated in patients with a cardiac rhythm disorder.

Measure heart rate prior to initiating treatment and periodically monitor the heart rate throughout SAVELLA treatment. Treat pre-existing tachyarrhythmias and other cardiac disease before starting therapy with SAVELLA. For patients who experience a sustained increase in heart rate while receiving SAVELLA, either reduce the dose or discontinue treatment with SAVELLA if clinically warranted.

5.5 Seizures

SAVELLA has not been systematically evaluated in patients with a seizure disorder. In clinical trials evaluating SAVELLA in patients with fibromyalgia, seizures/convulsions have not been reported. However, seizures have been reported infrequently in patients treated with SAVELLA for disorders other than fibromyalgia. SAVELLA should be prescribed with care in patients with a history of a seizure disorder.

5.6 Hepatotoxicity

In the placebo-controlled fibromyalgia trials, increases in the number of patients treated with SAVELLA with mild elevations of ALT or AST (1-3 times the upper limit of normal, ULN) were observed. Increases in ALT were more frequently observed in the patients treated with SAVELLA 100 mg/day (6%) and SAVELLA 200 mg/day (7%), compared to the patients treated with placebo (3%). One patient receiving SAVELLA 100 mg/day (0.2%) had an increase in ALT greater than 5 times the upper limit of normal but did not exceed 10 times the upper limit of normal. Increases in AST were more frequently observed in the patients treated with SAVELLA 100 mg/day (3%) and SAVELLA 200 mg/day (5%) compared to the patients treated with placebo (2%).

The increases of bilirubin observed in the fibromyalgia clinical trials were not clinically significant.

No case met the criteria of elevated ALT > 3x ULN and associated with an increase in bilirubin ≥ 2x ULN.

There have been cases of increased liver enzymes and reports of severe liver injury, including fulminant hepatitis with milnacipran from foreign postmarketing experience. In the cases of severe liver injury, there were significant underlying clinical conditions and/or the use of multiple concomitant medications. Because of underreporting, it is impossible to provide an accurate estimate of the true incidence of these reactions.

Discontinue SAVELLA in patients who develop jaundice or other evidence of liver dysfunction. Treatment with SAVELLA should not be resumed unless another cause can be established.

SAVELLA should ordinarily not be prescribed to patients with substantial alcohol use or evidence of chronic liver disease.

5.7 Discontinuation of Treatment with SAVELLA

Withdrawal symptoms have been observed in clinical trials following discontinuation of milnacipran, as with other SNRIs and SSRIs.

During marketing of milnacipran, and other SNRIs and SSRIs, there have been spontaneous reports of adverse events indicative of withdrawal and physical dependence occurring upon discontinuation of these drugs, particularly when discontinuation is abrupt. The adverse events include the following: dysphoric mood, irritability, agitation, dizziness, sensory disturbances (e.g., paresthesias such as electric shock sensations), anxiety, confusion, headache, lethargy, emotional lability, insomnia, hypomania, tinnitus, and seizures. Although these events are generally self-limiting, some have been reported to be severe.

Monitor patients for these symptoms when discontinuing treatment with SAVELLA. SAVELLA should be tapered after extended use. Do not abruptly discontinue. If intolerable symptoms occur following a decrease in the dose or upon discontinuation of treatment, then resuming the previously prescribed dose may be considered. Subsequently, the physician may continue decreasing the dose but at a more gradual rate [see Dosage and Administration (2.4)].

5.8 Hyponatremia

Hyponatremia may occur as a result of treatment with SSRIs and SNRIs, including SAVELLA. In many cases, this hyponatremia appears to be the result of the syndrome of inappropriate antidiuretic hormone secretion (SIADH). Cases with serum sodium lower than 110 mmol/L have been reported. Elderly patients may be at greater risk of developing hyponatremia with SNRIs, SSRIs, or SAVELLA. Also, patients taking diuretics or who are otherwise volume-depleted may be at greater risk [see Geriatric Use (8.5)]. Consider discontinuation of SAVELLA in patients with symptomatic hyponatremia.

Signs and symptoms of hyponatremia include headache, difficulty concentrating, memory impairment, confusion, weakness, and unsteadiness, which may lead to falls. Signs and symptoms associated with more severe and/or acute cases have included hallucination, syncope, seizure, coma, respiratory arrest, and death.

5.9 Increased Risk of Bleeding

Drugs that interfere with serotonin reuptake, including SAVELLA, may increase the risk of bleeding events. Concomitant use of aspirin, nonsteroidal anti-inflammatory drugs (NSAIDs), warfarin, and other anticoagulants may add to this risk. Case reports and epidemiological studies (case-control and cohort design) have demonstrated an association between use of drugs that interfere with serotonin reuptake and the occurrence of gastrointestinal bleeding. Based on data from published observational studies, exposure to SNRIs, particularly in the month before delivery, has been associated with a less than 2-fold increase in the risk of postpartum hemorrhage [see Use in Specific Populations (8.1)]. Bleeding events related to SSRIs and SNRIs have ranged from ecchymosis, hematoma, epistaxis, and petechiae to life-threatening hemorrhages.

Inform patients about the increased risk of bleeding associated with the concomitant use of SAVELLA and NSAIDs, aspirin, or other drugs that affect coagulation [see Drug Interactions (7.7)].

5.10 Activation of Mania

No activation of mania or hypomania was reported in the clinical trials evaluating effects of SAVELLA in patients with fibromyalgia. However, those clinical trials excluded patients with current major depressive episode. Activation of mania and hypomania have been reported in patients with mood disorders who were treated with other similar drugs for major depressive disorder. As with these other agents, use SAVELLA cautiously in patients with a history of mania.

5.11 Patients with a History of Dysuria

Because of their noradrenergic effect, SNRIs including SAVELLA, can affect urethral resistance and micturition. In the controlled fibromyalgia trials, dysuria occurred more frequently in patients treated with SAVELLA (1%) than in placebo-treated patients (0.5%). Caution is advised in use of SAVELLA in patients with a history of dysuria, notably in male patients with prostatic hypertrophy, prostatitis, and other lower urinary tract obstructive disorders. Male patients are more prone to genitourinary adverse effects, such as dysuria or urinary retention, and may experience testicular pain or ejaculation disorders.

5.12 Sexual Dysfunction

Use of SNRIs, including SAVELLA, may cause symptoms of sexual dysfunction [see Adverse Reactions (6.1, 6.2)]. In male patients, SNRI use may result in ejaculatory delay or failure, decreased libido, and erectile dysfunction. In female patients, SNRI use may result in decreased libido and delayed or absent orgasm.

It is important for prescribers to inquire about sexual function prior to initiation of SAVELLA and to inquire specifically about changes in sexual function during treatment, because sexual function may not be spontaneously reported. When evaluating changes in sexual function, obtaining a detailed history (including timing of symptom onset) is important because sexual symptoms may have other causes, including the underlying psychiatric disorder. Discuss potential management strategies to support patients in making informed decisions about treatment.

5.13 Angle Closure Glaucoma

The pupillary dilation that occurs following use of SNRI drugs including SAVELLA may trigger an angle closure attack in a patient with anatomically narrow angles who does not have a patent iridectomy.

5.14 Concomitant Use with Alcohol

In clinical trials, more patients treated with SAVELLA developed elevated transaminases than did placebo treated patients [see Warnings and Precautions (5.6)]. Because it is possible that milnacipran may aggravate pre-existing liver disease, SAVELLA should not be prescribed to patients with substantial alcohol use or evidence of chronic liver disease.

6 ADVERSE REACTIONS

6.1 Clinical Trials Experience

Because clinical trials are conducted under widely varying conditions, adverse reaction rates observed in the clinical trials of a drug cannot be directly compared to rates in the clinical trials of another drug and may not reflect the rates observed in practice.

Patient Exposure

SAVELLA was evaluated in three double-blind placebo-controlled trials involving 2209 fibromyalgia patients (1557 patients treated with SAVELLA and 652 patients treated with placebo) for a treatment period up to 29 weeks.

The stated frequencies of adverse reactions represent the proportion of individuals who experienced, at least once, a treatment-emergent adverse reaction of the type listed. A reaction was considered treatment emergent if it occurred for the first time or worsened while receiving therapy following baseline evaluation.

Adverse Reactions Leading to Discontinuation

In placebo-controlled trials in patients with fibromyalgia, 23% of patients treated with SAVELLA 100 mg/day, 26% of patients treated with SAVELLA 200 mg/day discontinued prematurely due to adverse reactions, compared to 12% of patients treated with placebo. The adverse reactions that led to withdrawal in ≥ 1% of patients in the SAVELLA treatment group and with an incidence rate greater than that in the placebo treatment group were nausea (milnacipran 6%, placebo 1%), palpitations (milnacipran 3%, placebo 1%), headache (milnacipran 2%, placebo 0%), constipation (milnacipran 1%, placebo 0%), heart rate increased (milnacipran 1%, placebo 0%), hyperhidrosis (milnacipran 1%, placebo 0%), vomiting (milnacipran 1%, placebo 0%), and dizziness (milnacipran 1% and placebo 0.5%). Discontinuation due to adverse reactions was generally more common among patients treated with SAVELLA 200 mg/day compared to SAVELLA 100 mg/day.

Most Common Adverse Reactions in Placebo Controlled Trials

In the placebo-controlled fibromyalgia patient trials, the most frequently occurring adverse reaction in clinical trials was nausea. The most common adverse reactions (incidence ≥ 5% and twice placebo) in patients treated with SAVELLA were constipation, hot flush, hyperhidrosis, vomiting, palpitations, heart rate increased, dry mouth, and hypertension.

Table 4 lists all adverse reactions that occurred in at least 2% of patients treated with SAVELLA at either 100 or 200 mg/day and at an incidence greater than that of placebo.

Table 4: Treatment-Emergent Adverse Reaction Incidence in Placebo Controlled Trials in Fibromyalgia Patients (Events Occurring in at Least 2% of All SAVELLA-Treated Patients and Occurring More Frequently in Either SAVELLA Treatment Group Than in the Placebo Treatment Group)
System Organ Class– Preferred Term | SAVELLA 100 mg/day (n = 623) % | SAVELLA 200 mg/day (n = 934) % | All SAVELLA (n = 1557) % | Placebo (n = 652) %
Cardiac Disorders
Palpitations | 8 | 7 | 7 | 2
Tachycardia | 3 | 2 | 2 | 1
Eye Disorders
Vision blurred | 1 | 2 | 2 | 1
Gastrointestinal Disorders
Nausea | 35 | 39 | 37 | 20
Constipation | 16 | 15 | 16 | 4
Vomiting | 6 | 7 | 7 | 2
Dry mouth | 5 | 5 | 5 | 2
Abdominal pain | 3 | 3 | 3 | 2
General Disorders
Chest pain | 3 | 2 | 2 | 2
Chills | 1 | 2 | 2 | 0
Chest discomfort | 2 | 1 | 1 | 1
Infections
Upper respiratory tract infection | 7 | 6 | 6 | 6
Investigations
Heart rate increased | 5 | 6 | 6 | 1
Blood pressure increased | 3 | 3 | 3 | 1
Metabolism and Nutrition Disorders
Decreased appetite | 1 | 2 | 2 | 0
Nervous System Disorders
Headache | 19 | 17 | 18 | 14
Dizziness | 11 | 10 | 10 | 6
Migraine | 6 | 4 | 5 | 3
Paresthesia | 2 | 3 | 2 | 2
Tremor | 2 | 2 | 2 | 1
Hypoesthesia | 1 | 2 | 1 | 1
Tension headache | 2 | 1 | 1 | 1
Psychiatric Disorders
Insomnia | 12 | 12 | 12 | 10
Anxiety | 5 | 3 | 4 | 4
Respiratory Disorders
Dyspnea | 2 | 2 | 2 | 1
Skin Disorders
Hyperhidrosis | 8 | 9 | 9 | 2
Rash | 3 | 4 | 3 | 2
Pruritus | 3 | 2 | 2 | 2
Vascular Disorders
Hot flush | 11 | 12 | 12 | 2
Hypertension | 7 | 4 | 5 | 2
Flushing | 2 | 3 | 3 | 1

Weight Changes

In placebo-controlled fibromyalgia clinical trials, patients treated with SAVELLA for up to 3 months experienced a mean weight loss of approximately 0.8 kg in both the SAVELLA 100 mg/day and the SAVELLA 200 mg/day treatment groups, compared with a mean weight loss of approximately 0.2 kg in placebo-treated patients.

Genitourinary Adverse Reactions in Males

In the placebo-controlled fibromyalgia studies, the following treatment-emergent adverse reactions related to the genitourinary system were observed in at least 2% of male patients treated with SAVELLA, and occurred at a rate greater than in placebo-treated male patients: dysuria, ejaculation disorder, erectile dysfunction, ejaculation failure, libido decreased, prostatitis, scrotal pain, testicular pain, testicular swelling, urinary hesitation, urinary retention, urethral pain, and urine flow decreased.

Other Adverse Reactions Observed During Clinical Trials of SAVELLA in Fibromyalgia

Following is a list of frequent (those occurring on one or more occasions in at least 1/100 patients) treatment-emergent adverse reactions reported from 1824 fibromyalgia patients treated with SAVELLA for periods up to 68 weeks. The listing does not include those events already listed in Table 4, those events for which a drug cause was remote, those events which were so general as to be uninformative, and those events reported only once which did not have a substantial probability of being acutely life threatening.

Adverse reactions are categorized by body system and listed in order of decreasing frequency. Adverse reactions of major clinical importance are described in the Warnings and Precautions section (5).

Gastrointestinal Disorders ― diarrhea, dyspepsia, gastroesophageal reflux disease, flatulence, abdominal distension
General Disorders ― fatigue, peripheral edema, irritability, pyrexia
Infections ― urinary tract infection, cystitis
Injury, Poisoning, and Procedural Complications ― contusion, fall
Investigations ― weight decreased or increased
Metabolism and Nutrition Disorders ― hypercholesterolemia
Nervous System Disorders ― somnolence, dysgeusia
Psychiatric Disorders ― depression, stress
Skin Disorders ― night sweats

6.2 Postmarketing Experience

The following additional adverse reactions have been identified from spontaneous reports of SAVELLA received worldwide. These adverse reactions have been chosen for inclusion because of a combination of seriousness, frequency of reporting, or potential causal connection to SAVELLA. However, because these adverse reactions were reported voluntarily from a population of uncertain size, it is not always possible to reliably estimate their frequency or establish a causal relationship to drug exposure. These events include:

Blood and Lymphatic System Disorders ― leukopenia, neutropenia, thrombocytopenia
Cardiac Disorders ― supraventricular tachycardia, Takotsubo cardiomyopathy
Eye Disorders ― accommodation disorder
Endocrine Disorders ― hyperprolactinemia
Gastrointestinal Disorders ― acute pancreatitis
Hepatobiliary Disorders ― hepatitis
Metabolism and Nutrition Disorders ― anorexia, hyponatremia
Musculoskeletal and Connective Tissue Disorders ― rhabdomyolysis
Nervous System Disorders ― anosmia, convulsions (including grand mal), hyposmia, loss of consciousness, Parkinsonism
Psychiatric Disorders ― aggression, anger, delirium, hallucination, homicidal ideation
Renal and Urinary Disorders ― acute renal failure
Reproductive System and Breast Disorders ― galactorrhea, decreased libido, delayed or absent orgasm
Skin Disorders ― erythema multiforme, Stevens Johnson syndrome
Vascular Disorders ― hypertensive crisis

7 DRUG INTERACTIONS

Milnacipran undergoes minimal CYP450 related metabolism, with the majority of the dose excreted unchanged in urine (55%) and has a low binding to plasma proteins (13%). In vitro and in vivo studies showed that SAVELLA is unlikely to be involved in clinically significant pharmacokinetic drug interactions [see Pharmacokinetics in Special Populations (12.3)].

7.1 Monoamine Oxidase Inhibitors (MAOIs)

The concomitant use of SSRIs and SNRIs, including SAVELLA, with MAOIs increases the risk of serotonin syndrome. The use of MAOIs intended to treat psychiatric disorders with SAVELLA or within 5 days of stopping treatment with SAVELLA is contraindicated. The use of SAVELLA within 14 days of stopping an MAOI intended to treat psychiatric disorders is also contraindicated. In addition, do not initiate SAVELLA in a patient who is being treated with MAOIs such as linezolid or intravenous methylene blue. No reports involved the administration of methylene blue by other routes (such as oral tablets or local tissue injection). If it is necessary to initiate treatment with a MAOI such as linezolid or intravenous methylene blue in a patient taking SAVELLA, discontinue SAVELLA before initiating treatment with the MAOI [see Dosage and Administration (2.5, 2.6), Contraindications (4), Drug Interactions (7.1)].

7.2 Serotonergic Drugs

Serotonin syndrome can occur with use of SAVELLA and other serotonergic drugs (other SNRIs, SSRIs, triptans, tricyclic antidepressants, opioids, lithium, tryptophan, buspirone, amphetamines, and St. John’s Wort), or with drugs that impair metabolism of serotonin (i.e., monoamine oxidase inhibitors). Advise patients of the signs and symptoms associated with serotonin syndrome and to seek medical care immediately if they experience these symptoms [see Dosage and Administration (2.5, 2.6), Warnings and Precautions (5.2)].

7.3 Triptans

There have been rare postmarketing reports of serotonin syndrome with use of an SSRI and a triptan. If concomitant treatment of SAVELLA with a triptan is clinically warranted, careful observation of the patient is advised, particularly during treatment initiation and dose increases [see Warnings and Precautions (5.2)].

7.4 Catecholamines

SAVELLA inhibits the reuptake of norepinephrine. Therefore, concomitant use of SAVELLA with epinephrine and norepinephrine may be associated with paroxysmal hypertension and possible arrhythmia [see Warnings and Precautions (5.3, 5.4)].

7.5 CNS-active drugs

Given the primary CNS effects of SAVELLA, use caution when it is taken in combination with other centrally acting drugs, including those with a similar mechanism of action.

Clomipramine: In a drug-drug interaction study, an increase in euphoria and postural hypotension was observed in patients who switched from clomipramine to SAVELLA.

7.6 Clinically Important Interactions with Select Cardiovascular Agents

Digoxin: Use of SAVELLA concomitantly with digoxin may be associated with potentiation of adverse hemodynamic effects. Postural hypotension and tachycardia have been reported in combination therapy with intravenously administered digoxin (1 mg). Avoid co-administration of SAVELLA and intravenous digoxin [see Warnings and Precautions (5.3, 5.4)].

Clonidine: Because SAVELLA inhibits norepinephrine reuptake, co-administration with clonidine may inhibit clonidine’s anti-hypertensive effect.

7.7 Drugs that Interfere with Hemostasis

Concomitant use of SAVELLA with an antiplatelet or anticoagulant drug (e.g., NSAIDs, aspirin, and warfarin) may potentiate the risk of bleeding. This may be due to the effect of SAVELLA on the release of serotonin by platelets. Closely monitor for bleeding for patients receiving an antiplatelet or anticoagulant drug when SAVELLA is initiated or discontinued [see Warnings and Precautions (5.9)].

8 USE IN SPECIFIC POPULATIONS

8.1 Pregnancy

Risk Summary

Based on data from published observational studies, exposure to SNRIs, particularly in the month before delivery, has been associated with a less than 2-fold increase in the risk of postpartum hemorrhage [see Warnings and Precautions (5.2)].

The available data on SAVELLA use in pregnant women are insufficient to evaluate for a drug-associated risk of major birth defects, miscarriage, or adverse maternal or fetal outcomes. There are risks associated with exposure to serotonin and norepinephrine reuptake inhibitors (SNRIs) and selective-serotonin reuptake inhibitors (SSRIs), including SAVELLA, during pregnancy (see Clinical Considerations). Animal reproduction studies have been performed in rats, rabbits and mice. Milnacipran was shown to increase embryofetal and perinatal lethality in rats and the incidence of a minor skeletal variation in rabbits at doses below (rat) or approximately equal to (rabbit) the maximum recommended human dose (MRHD) of 200 mg/day on a mg/m^2 basis. No effects were seen in mice when treated with milnacipran during the period of organogenesis at doses up to 3 times the MHRD on a mg/m^2 basis (see Data).

The estimated background risk of major birth defects and miscarriage for the indicated population is unknown. All pregnancies have a background risk of birth defect, loss, or other adverse outcomes. In the U.S. general population, the estimated background risk of major birth defects and miscarriage in clinically recognized pregnancies is 2%-4% and 15%-20%, respectively.

Clinical Consideration

Maternal adverse reactions

Use of SAVELLA in the month before delivery may be associated with an increased risk of postpartum hemorrhage [see Warnings and Precautions (5.9)].

Fetal/Neonatal adverse reactions

Neonates exposed to SNRIs or SSRIs, including SAVELLA, late in the third trimester have developed complications requiring prolonged hospitalization, respiratory support, and tube feeding. Such complications can arise immediately upon delivery.

Reported clinical findings have included respiratory distress, cyanosis, apnea, seizures, temperature instability, feeding difficulty, vomiting, hypoglycemia, hypotonia, hypertonia, hyperreflexia, tremor, jitteriness, irritability, and constant crying. These findings are consistent with either direct toxic effect of SSRIs and SNRIs or possibly, a drug discontinuation syndrome. It should be noted that, in some cases, the clinical picture is consistent with serotonin syndrome [see Warnings and Precautions (5.2, 5.7)].

Data

Animal Data

Studies were conducted in rats, rabbits and mice with dosing of milnacipran during the period of organogenesis. In rats, milnacipran was shown to increase embryofetal lethality at doses of 5 mg/kg/day (0.25 times the MRHD on a mg/m^2 basis). In rabbits, dose-dependent increases in the incidence of the skeletal variation of an extra single rib were observed in several pups from multiple litters in the absence of maternal toxicity at 15 mg/kg/day (1.5 times the MRHD on a mg/m^2 basis). The clinical significance of this finding is unknown. In mice, no embryotoxic or teratogenic effects were seen at doses up to 125 mg/kg/day (3 times the MHRD on a mg/m^2 basis).

With peri- and postnatal exposure to oral milnacipran in rats, decreases in viability and body weight were observed on Postpartum Day 4 at a dose of 5 mg/kg/day (approximately 0.25 times the MRHD on a mg/m^2 basis). The no-effect dose for maternal and offspring toxicity was 2.5 mg/kg/day (approximately 0.1 times the MRHD on a mg/m^2 basis).

8.2 Lactation

Risk Summary

Milnacipran is present in human milk [see Data]. There are no reports on the effects of milnacipran on the breastfed child and on milk production/excretion. However, there are reports of agitation, irritability, poor feeding, and poor weight gain in infants exposed to SSRIs or SNRIs through breast milk (see Clinical Considerations).

The developmental and health benefits of breastfeeding should be considered along with the mother’s clinical need for SAVELLA and any potential adverse effects on the breastfed child from SAVELLA or from the underlying maternal conditions.

Clinical Considerations

Monitor infants exposed to milnacipran for agitation, irritability, poor feeding and poor weight gain.

Data

Human Data

Milnacipran is present in the milk of lactating women treated with milnacipran. In a lactation pharmacokinetic study with milnacipran, a single, oral dose of 50 mg milnacipran HCl tablet was administered to 8 lactating women who were at least 12 weeks postpartum and weaning their infants. The milk/plasma AUC ratio of milnacipran was 1.85 ± 0.38. The maximum estimated weight adjusted daily infant dose for milnacipran from breast milk (assuming mean milk consumption of 150 mL/kg/day) was 5% of the maternal dose based on peak plasma concentrations.

8.4 Pediatric Use

Safety and effectiveness of SAVELLA in a fibromyalgia pediatric population below the age of 18 have not been established [see Boxed Warning, Indications and Usage (1), and Warnings and Precautions (5.1)]. The use of SAVELLA is not recommended in pediatric patients.

8.5 Geriatric Use

In controlled clinical studies of SAVELLA, 402 patients were 60 years or older, and no overall differences in safety and efficacy were observed between these patients and younger patients.

In view of the predominant excretion of unchanged milnacipran via kidneys and the expected decrease in renal function with age, renal function should be considered prior to use of SAVELLA in the elderly [see Dosage and Administration (2.2)].

SNRIs, SSRIs, and SAVELLA, have been associated with cases of clinically significant hyponatremia in elderly patients, who may be at greater risk for this adverse event [see Warnings and Precautions (5.8)].

9 DRUG ABUSE AND DEPENDENCE

9.1 Controlled Substance

Milnacipran is not a controlled substance.

9.2 Abuse

Milnacipran did not produce behavioral signs indicative of abuse potential in animal or human studies.

9.3 Dependence

Milnacipran produces physical dependence, as evidenced by the emergence of withdrawal symptoms following drug discontinuation, similar to other SNRIs and SSRIs. These withdrawal symptoms can be severe. Thus, taper SAVELLA and do not abruptly discontinue after extended use [see Warnings and Precautions (5.7)].

10 OVERDOSAGE

Clinical Presentation

There is limited clinical experience with SAVELLA overdose in humans. In clinical trials, cases of acute ingestions up to 1000 mg, alone or in combination with other drugs, were reported with none being fatal.

In postmarketing experience, fatal outcomes have been reported for acute overdoses primarily involving multiple drugs but also with SAVELLA only. The most common signs and symptoms included increased blood pressure, cardio-respiratory arrest, changes in the level of consciousness (ranging from somnolence to coma), confusional state, dizziness, and increased hepatic enzymes.

Management of Overdose

There is no specific antidote to SAVELLA, but if serotonin syndrome ensues, specific treatment (such as with cyproheptadine and/or temperature control) may be considered. In case of acute overdose, treatment should consist of those general measures employed in the management of overdose with any drug.

Ensure adequate airway, oxygenation, and ventilation and monitor cardiac rhythm and vital signs. Induction of emesis is not recommended. Gastric lavage with a large-bore orogastric tube with appropriate airway protection, if needed, may be indicated if performed soon after ingestion or in symptomatic patients. Because there is no specific antidote for SAVELLA, consider symptomatic care and treatment with gastric lavage and activated charcoal as soon as possible for patients who experience a SAVELLA overdose.

Due to the large volume of distribution of this drug, forced diuresis, dialysis, hemoperfusion, and exchange transfusion are unlikely to be beneficial.

In managing overdose, consider the possibility of multiple drug involvement. The physician should consider contacting a poison control center for additional information on the treatment of any overdose. Telephone numbers for certified poison control centers are listed in the Physicians’ Desk Reference (PDR).

11 DESCRIPTION

Milnacipran hydrochloride is a selective norepinephrine and serotonin reuptake inhibitor; it inhibits norepinephrine uptake with greater potency than serotonin. It is a racemic mixture with the chemical name: (±)-[1R(S),2S(R)]-2-(aminomethyl)-N,N-diethyl-1-phenylcyclopropanecarboxamide hydrochloride. The structural formula is:

Milnacipran hydrochloride is a white to off-white crystalline powder with a melting point of 179°C.

It is freely soluble in water, methanol, ethanol, chloroform, and methylene chloride and sparingly soluble in diethyl ether. It has an empirical formula of C15H23ClN2O and a molecular weight of 282.8 g/mol.

SAVELLA is available for oral administration as film-coated tablets containing 12.5 mg, 25 mg, 50 mg, and 100 mg milnacipran hydrochloride. Each tablet also contains dibasic calcium phosphate, povidone, carboxymethylcellulose calcium, colloidal silicon dioxide, magnesium stearate, and talc as inactive ingredients. The film coat contains the following additional inactive ingredients:

12.5 mg:

FD&C Blue #2 Aluminum Lake, polyvinyl alcohol, polyethylene glycol, titanium dioxide

25 mg:

Polyvinyl alcohol, polyethylene glycol, titanium dioxide

50 mg:

Polyvinyl alcohol, polyethylene glycol, titanium dioxide

100 mg:

FD&C Red #40 Aluminum Lake, polyvinyl alcohol, polyethylene glycol, titanium dioxide

12 CLINICAL PHARMACOLOGY

12.1 Mechanism of Action

The exact mechanism of the central pain inhibitory action of milnacipran and its ability to improve the symptoms of fibromyalgia in humans are unknown. Preclinical studies have shown that milnacipran is a potent inhibitor of neuronal norepinephrine and serotonin reuptake; milnacipran inhibits norepinephrine uptake with approximately 3-fold higher potency in vitro than serotonin without directly affecting the uptake of dopamine or other neurotransmitters. Milnacipran has no significant affinity for serotonergic (5-HT1-7), α- and β-adrenergic, muscarinic (M1-5), histamine (H1-4), dopamine (D1-5), opiate, benzodiazepine, and γ-aminobutyric acid (GABA) receptors in vitro. Pharmacologic activity at these receptors is hypothesized to be associated with the various anticholinergic, sedative, and cardiovascular effects seen with other psychotropic drugs.

Milnacipran has no significant affinity for Ca++, K+, Na+ and Cl– channels and does not inhibit the activity of human monoamine oxidases (MAO-A and MAO-B) or acetylcholinesterase.

12.2 Pharmacodynamics

Cardiac Electrophysiology

The effect of SAVELLA on the QTcF interval was measured in a double-blind placebo- and positive-controlled parallel study in 88 healthy subjects using 600 mg/day SAVELLA (3 to 6 times the recommended therapeutic dose for fibromyalgia). After baseline and placebo adjustment, the maximum mean QTcF change was 8 ms (2-sided 90% CI, 3-12 ms). This increase is not considered to be clinically significant.

12.3 Pharmacokinetics

Milnacipran is well absorbed after oral administration with an absolute bioavailability of approximately 85% to 90%. The exposure to milnacipran increased proportionally within the therapeutic dose range. It is excreted predominantly unchanged in urine (55%) and has a terminal elimination half-life of about 6 to 8 hours. Steady-state levels are reached within 36 to 48 hours and can be predicted from single-dose data. The active enantiomer, d-milnacipran, has a longer elimination half-life (8-10 hours) than the l-enantiomer (4-6 hours). There is no interconversion between the enantiomers.

Absorption

SAVELLA is absorbed following oral administration with maximum concentrations (Cmax) reached within 2 to 4 hours post dose. Absorption of SAVELLA is not affected by food. The absolute bioavailability is approximately 85% to 90%.

Distribution

The mean volume of distribution of milnacipran following a single intravenous dose to healthy subjects is approximately 400 L.

Plasma protein binding is 13%.

Elimination

Metabolism

Milnacipran and its metabolites are eliminated primarily by renal excretion.

Excretion

Following oral administration of ^14C-milnacipran hydrochloride, approximately 55% of the dose was excreted in urine as unchanged milnacipran (24% as l-milnacipran and 31% as d-milnacipran). The l-milnacipran carbamoyl-O-glucuronide was the major metabolite excreted in urine and accounted for approximately 17% of the dose; approximately 2% of the dose was excreted in urine as d-milnacipran carbamoyl-O-glucuronide. Approximately 8% of the dose was excreted in urine as the N-desethyl milnacipran metabolite.

Specific Populations

Geriatric Patients

Cmax and AUC parameters of milnacipran were about 30% higher in elderly (> 65 years) subjects compared with young subjects due to age-related decreases in renal function.

No dosage adjustment is necessary based on age unless renal function is severely impaired [see Dosage and Administration (2.2)].

Male and Female Patients

Cmax and AUC parameters of milnacipran were about 20% higher in female subjects compared with male subjects. Dosage adjustment based on gender is not necessary.

Patients with Renal Impairment

Milnacipran pharmacokinetics were evaluated following single oral administration of 50 mg SAVELLA to subjects with mild (creatinine clearance [CLcr] 50-80 mL/min), moderate (CLcr 30-49 mL/min), and severe (CLcr 5-29 mL/min) renal impairment and to healthy subjects (CLcr > 80 mL/min). The mean AUC0-∞ increased by 16%, 52%, and 199%, and terminal elimination half-life increased by 38%, 41%, and 122% in subjects with mild, moderate, and severe renal impairment, respectively, compared with healthy subjects.

No dosage adjustment is necessary for patients with mild renal impairment. Exercise caution in patients with moderate renal impairment. Dose adjustment is necessary in severe renal impairment patients [see Dosage and Administration (2.2)].

Patients with Hepatic Impairment

Milnacipran pharmacokinetics were evaluated following single oral administration of 50 mg SAVELLA to subjects with mild (Child-Pugh A), moderate (Child-Pugh B), and severe (Child-Pugh C) hepatic impairment and to healthy subjects. AUC0-∞ and T½ were similar in healthy subjects and subjects with mild and moderate hepatic impairment. However, subjects with severe hepatic impairment had a 31% higher AUC0-∞ and a 55% higher T½ than healthy subjects. Exercise caution in patients with severe hepatic impairment.

Drug Interaction Studies

In Vitro Studies:

In general, milnacipran, at concentrations that were at least 25 times those attained in clinical trials, did not inhibit human CYP1A2, CYP2A6, CYP2C9, CYP2C19, CYP2D6, CYP2E1, and CYP3A4 or induce human CYP1A2, CYP2B6, CYP2C8, CYP2C9, CYP2C19, and CYP3A4/5 enzyme systems, indicating a low potential of interactions with drugs metabolized by these enzymes.

In vitro studies have shown that the biotransformation rate of milnacipran by human hepatic microsomes and hepatocytes was low. A low biotransformation was also observed following incubation of milnacipran with cDNA-expressed human CYP1A2, CYP2A6, CYP2B6, CYP2C9, CYP2C19, CYP2D6, CYP2E1, and CYP3A4 isozymes.

In Vivo Studies:

The drug interaction studies described in this section were conducted in healthy adult subjects.

Carbamazepine- There were no clinically significant changes in the pharmacokinetics of milnacipran following co-administration of SAVELLA (100 mg/day) and carbamazepine (200 mg twice a day). No changes were observed in the pharmacokinetics of carbamazepine or its epoxide metabolite due to co-administration with SAVELLA.

Clomipramine- Switching from clomipramine (75 mg once a day) to milnacipran (100 mg/day) without a washout period did not lead to clinically significant changes in the pharmacokinetics of milnacipran. Because an increase in adverse events (eg, euphoria and postural hypotension) was observed after switching from clomipramine to milnacipran, monitoring of patients during treatment switch is recommended.

Digoxin- There was no pharmacokinetic interaction between SAVELLA (200 mg/day) and digoxin (0.2 mg/day Lanoxicaps) following multiple-dose administration to healthy subjects.

Fluoxetine- Switching from fluoxetine (20 mg once a day), a strong inhibitor of CYP2D6 and a moderate inhibitor of CYP2C19, to milnacipran (100 mg/day) without a washout period did not affect the pharmacokinetics of milnacipran.

Lithium- Multiple doses of SAVELLA (100 mg/day) did not affect the pharmacokinetics of lithium.

Lorazepam- There was no pharmacokinetic interaction between a single dose of SAVELLA (50 mg) and lorazepam (1.5 mg).

Pregabalin- There were no clinically significant changes in the steady-state pharmacokinetics of milnacipran or pregabalin following twice a day co-administration of 50 mg milnacipran and 150 mg pregabalin.

Warfarin- Steady-state milnacipran (200 mg/day) did not affect the pharmacokinetics of R-warfarin and S-warfarin or the pharmacodynamics (as assessed by measurement of prothrombin INR) of a single dose of 25 mg warfarin. The pharmacokinetics of SAVELLA were not altered by warfarin.

13 NONCLINICAL TOXICOLOGY

13.1 Carcinogenesis, Mutagenesis, Impairment of Fertility

Carcinogenesis

Dietary administration of milnacipran to rats at doses of 50 mg/kg/day (2 times the MRHD on a mg/m^2 basis) for 2 years caused a statistically significant increase in the incidence of thyroid C-cell adenomas and combined adenomas and carcinomas in males. A carcinogenicity study was conducted in Tg.rasH2 mice for 6 months at oral gavage doses of up to 125 mg/kg/day.

Milnacipran did not induce tumors in Tg.rasH2 mice at any dose tested.

Mutagenesis

Milnacipran was not mutagenic in the in vitro bacterial reverse mutation assay (Ames test) or in the L5178Y TK +/- mouse lymphoma forward mutation assay. Milnacipran was also not clastogenic in an in vitro chromosomal aberration test in human lymphocytes or in the in vivo mouse micronucleus assay.

Impairment of Fertility

Although administration of milnacipran to male and female rats had no statistically significant effect on mating or fertility at doses up to 80 mg/kg/day (4 times the MRHD on an mg/m^2 basis), there was an apparent dose-related decrease in the fertility index at clinically relevant doses based on body surface area.

13.2 Animal Toxicology and/or Pharmacology

Hepatic Effects

Chronic administration (2 years) of milnacipran to rats at 15 mg/kg (0.6 times the MRHD on an mg/m^2 basis) and higher doses showed increased incidences of centrilobular vacuolation of the liver in male rats and eosinophilic foci in male and female rats in the absence of any change in hepatic enzymes. The clinical significance of the finding is not known. Chronic (1 year) administration in the primate at doses up to 25 mg/kg (2 times the MRHD on a mg/m^2 basis) did not demonstrate similar evidence of hepatic changes.

Ocular Effects

Chronic (2 years) administration of milnacipran to rats at 15 mg/kg (0.6 times the MRHD on a mg/m^2 basis) and higher doses showed increased incidence of keratitis of the eye. One-year studies in the rat and primate did not show this response.

14 CLINICAL STUDIES

Management of Fibromyalgia

The efficacy of SAVELLA for the management of fibromyalgia was established in two double-blind, placebo-controlled, multicenter studies in adult patients (18-74 years of age). Enrolled patients met the American College of Rheumatology (ACR) criteria for fibromyalgia (a history of widespread pain for 3 months and pain present at 11 or more of the 18 specific tender point sites). Approximately 35% of patients had a history of depression. Study 1 was six months in duration and Study 2 was three months in duration.

A larger proportion of patients treated with SAVELLA than with placebo experienced a simultaneous reduction in pain from baseline of at least 30% (VAS) and also rated themselves as much improved or very much improved based on the patient global assessment (PGIC). In addition, a larger proportion of patients treated with SAVELLA met the criteria for treatment response, as measured by the composite endpoint that concurrently evaluated improvement in pain (VAS), physical function (SF-36 PCS), and patient global assessment (PGIC), in fibromyalgia as compared to placebo.

Study 1: This 6-month study compared total daily doses of SAVELLA 100 mg and 200 mg to placebo. Patients were enrolled with a minimum mean baseline pain score of ≥ 50 mm on a 100 mm visual analog scale (VAS) ranging from 0 (“no pain”) to 100 (“worst possible pain”). The mean baseline pain score in this trial was 69. The efficacy results for Study 1 are summarized in Figure 1.

Figure 1 shows the proportion of patients achieving various degrees of improvement in pain from baseline to the 3-month time point and who concurrently rated themselves globally improved (PGIC score of 1 or 2). Patients who did not complete the 3-month assessment were assigned 0% improvement. More patients in the SAVELLA treatment arms experienced at least a 30% reduction in pain from baseline (VAS) and considered themselves globally improved (PGIC) than did patients in the placebo arm. Treatment with SAVELLA 200 mg/day did not confer greater benefit than treatment with SAVELLA 100 mg/day.

Figure 1: Patients Achieving Various Levels of Pain Relief with Concurrent Ratings of Being Much or Very Much Improved on the PGIC ― Study 1

Study 2: This 3-month study compared total daily doses of SAVELLA 100 mg and 200 mg to placebo. Patients were enrolled with a minimum mean baseline pain score of ≥ 40 mm on a 100-mm VAS ranging from 0 (“no pain”) to 100 (“worst possible pain”). The mean baseline pain score in this trial was 65. The efficacy results for Study 2 are summarized in Figure 2.

Figure 2 shows the proportion of patients achieving various degrees of improvement in pain from baseline to the 3-month time point and who concurrently rated themselves globally improved (PGIC score of 1 or 2). Patients who did not complete the 3-month assessment were assigned 0% improvement. More patients in the SAVELLA treatment arms experienced at least a 30% reduction in pain from baseline (VAS) and considered themselves globally improved (PGIC) than did patients in the placebo arm. Treatment with SAVELLA 200 mg/day did not confer greater benefit than treatment with SAVELLA 100 mg/day.

Figure 2: Patients Achieving Various Levels of Pain Relief with Concurrent Ratings of Being Much or Very Much Improved on the PGIC ― Study 2

In both studies, some patients who rated themselves as globally “much” or “very much” improved experienced a decrease in pain as early as week 1 of treatment with a stable dose of SAVELLA that persisted throughout these studies.

16 HOW SUPPLIED/STORAGE AND HANDLING

50-mg tablets:

White, oval-shaped, film-coated tablets, debossed with “FL” on one side and “50” on the reverse side

Bottles of approximately 1920 film-coated tablets, NDC 55154-4626-8

Storage

Store at 25°C (77°F); excursions permitted between 15°C and 30°C (between 59°F and 86°F) [See USP Controlled Room Temperature].

17 PATIENT COUNSELING INFORMATION

Advise the patient to read the FDA-approved patient labeling (Medication Guide).

Advise patients of the following issues and to alert their prescriber if these occur while taking SAVELLA:

Clinical Worsening and Suicide Risk

Advise patients, their families, and their caregivers that patients with depression may be at increased risk for clinical worsening and/or suicidal ideation if they stop taking anti-depressant medication, change the dose, or start a new medication.

Encourage patients, their families, and their caregivers to be alert to the emergence of anxiety, agitation, panic attacks, insomnia, irritability, hostility, aggressiveness, impulsivity, akathisia (psychomotor restlessness), hypomania, or other unusual changes in behavior, worsening of depression, and suicidal ideation, especially early during treatment with SAVELLA or other drugs that inhibit the reuptake of norepinephrine and/or serotonin, and when the dose is adjusted up or down. Advise families and caregivers to observe for the emergence of such symptoms on a day-to-day basis, since changes may be abrupt and to report such symptoms to the patient’s prescriber or health professional, especially if they are severe, abrupt in onset, or were not part of the patient’s presenting symptoms [see Boxed Warning and Warnings and Precautions (5.1)].

Serotonin Syndrome

Inform patients about the risk of serotonin syndrome with use of SAVELLA as well as the increased risk when taken concomitantly with other serotonergic drugs including triptans, tricyclic antidepressants, opioids, lithium, tryptophan, buspirone, amphetamines and St. John’s Wort, and with drugs that impair metabolism of serotonin (in particular MAOIs, both those intended to treat psychiatric disorders and also others, such as linezolid) [see Warnings and Precautions (5.2), Drug Interactions (7.2)].

Advise patients of the signs and symptoms associated with serotonin syndrome and to seek medical care immediately if they experience these symptoms.

Elevated Blood Pressure and Heart Rate

Advise patients that SAVELLA may increase their blood pressure and heart rate and that they should have their blood pressure and heart rate monitored at regular intervals when receiving treatment with SAVELLA [see Warnings and Precautions (5.3, 5.4)].

Increased Risk of Bleeding

Advise patients that the concomitant use of drugs that interfere with serotonin reuptake, including SAVELLA, and NSAIDs, aspirin, or anticoagulants has been associated with an increased risk of abnormal bleeding [see Warnings and Precautions (5.9)].

Angle Closure Glaucoma

Advise patients that taking SAVELLA can cause mild pupillary dilation which, in susceptible individuals, can lead to an episode of angle closure glaucoma. [see Warnings and Precautions (5.13)].

Ability to Drive and Use Machinery

Advise patients not to operate machinery or drive motor vehicles until they are reasonably certain that SAVELLA treatment does not affect their ability to engage in such activities.

Alcohol

Inform patients of the risks associated with drinking alcohol while taking SAVELLA [see Warnings and Precautions (5.6, 5.14)].

Sexual Dysfunction

Advise patients that use of SAVELLA may cause symptoms of sexual dysfunction in both male and female patients. Inform patients that they should discuss any changes in sexual function and potential management strategies with their healthcare provider [see Warnings and Precautions (5.12)].

Discontinuation

Advise patients that withdrawal symptoms can occur when discontinuing treatment with SAVELLA, particularly when discontinuation is abrupt [see Warnings and Precautions (5.7)].

Missing a Dose

Advise patients that if they miss a dose, they should skip the missed dose and take the next dose at their regular time.

Pregnancy

- Advise pregnant women to notify their healthcare provider if they become pregnant or intend to become pregnant during treatment with SAVELLA.
- Advise patients that SAVELLA may increase the risk of neonatal complications requiring prolonged hospitalization, respiratory support, and tube feeding.

Lactation

Advise breastfeeding women using SAVELLA to monitor infants for sedation, agitation, irritability, poor feeding, and poor weight gain and to seek medical care if they notice these signs [see Use in Specific Populations (8.2)].

Distributed by:

AbbVie Inc.
1 N Waukegan Rd.
North Chicago, IL 60064

Licensed from Pierre Fabre Medicament

© 2025 AbbVie. All rights reserved.

SAVELLA and its design are trademarks of Allergan Sales, LLC, an AbbVie company.

Distributed By:

Cardinal Health

Dublin, OH 43017

ER7800 Rev. D

20091024

FDA-Approved Medication Guide

MEDICATION GUIDE
SAVELLA® (Sa-vel-la)
(milnacipran HCl)
Tablets

SAVELLA is not used to treat depression, but it acts like medicines that are used to treat depression (antidepressants) and other psychiatric disorders.
Read the Medication Guide that comes with SAVELLA® before you start taking it and each time you get a refill. There may be new information. This Medication Guide does not take the place of talking to your healthcare provider about your medical condition or treatment. Talk with your healthcare provider if there is something you do not understand or want to learn more about.
What is the most important information I should know about SAVELLA?
SAVELLA and antidepressant medicines may cause serious side effects, including:
1. Suicidal thoughts or actions:

- SAVELLA and antidepressant medicines may increase suicidal thoughts or actions in some children, teenagers, and young adults within the first few months of treatment or when the dose is changed.
- Depression or other serious mental illnesses are the most important causes of suicidal thoughts or actions. Watch for these changes and call your healthcare provider right away if you notice:
  - New or sudden changes, in mood, behavior, thoughts, or feelings, especially if severe.
  - Pay particular attention to such changes when SAVELLA is started or when the dose is changed.
  - Keep all follow-up visits with your healthcare provider and call between visits if you are worried about symptoms.

Call your healthcare provider right away or go to the nearest hospital emergency room if you have any of the following symptoms, especially if they are new, worse, or worry you:

• attempts to commit suicide

• feeling agitated, restless, angry or irritable

• acting on dangerous impulses

• trouble sleeping (insomnia)

• acting aggressive, being angry, or violent

• an increase in activity or talking more than what is normal for you

• thoughts about suicide or dying

• other unusual changes in behavior or mood

• new or worse depression

• new or worse anxiety or panic attacks

Call your healthcare provider right away or go to the nearest hospital emergency room if you have any symptoms of the serious side effects listed below:
2. Serotonin Syndrome. This condition can be life-threatening, symptoms may include:

- agitation, hallucinations, coma or other changes in mental status
- coordination problems or muscle twitching (overactive reflexes)
- sweating or fever
- diarrhea
- muscle rigidity
- dizziness
- tremor

Symptoms such as racing heartbeat, high or low blood pressure, nausea, vomiting, and flushing are common with SAVELLA. Call your healthcare provider right away if you get these symptoms and they are severe or if they happen with any of the symptoms of serotonin syndrome listed above.
3. Increase in blood pressure or heart rate: SAVELLA may increase your blood pressure or heart rate. Check your blood pressure and heart rate before you start and during treatment with SAVELLA. Before taking SAVELLA, tell your healthcare provider if you have high blood pressure or problems with your heart or blood vessels (cardiovascular disease).
4. Seizures or convulsions.
5. Liver problems. Symptoms of liver problems may include:

- itching
- right upper abdominal pain
- dark urine
- yellowing of your skin or eyes
- enlarged liver
- increased liver enzymes

6. Low salt (sodium) levels in the blood. Elderly people may be at greater risk for this. Symptoms may include:

- headache
- weakness or feeling unsteady
- confusion, problems concentrating or thinking or memory problems

7. Abnormal bleeding: SAVELLA and other similar medicines (antidepressants) may increase your risk of bleeding or bruising, especially if you take the blood thinner warfarin (Coumadin, Jantoven), a nonsteroidal anti-inflammatory drug (NSAID), or aspirin.
8. Manic episodes

- greatly increased energy
- severe trouble sleeping
- racing thoughts
- reckless behavior
- unusually grand ideas
- excessive happiness or irritability
- talking more or faster than usual

9. Problems with urination

- decreased urine flow
- unable to pass any urine
  Men may be more likely to have these symptoms, and may develop pain in their testicles or have problems with ejaculation.

10. Visual problems

- eye pain
- changes in vision
- swelling or redness in or around eye

Only some people are at risk for these problems. You may want to undergo an eye examination to see if you are at risk and receive preventative treatment if you are.
11. Sexual problems (dysfunction). Taking serotonin and norepinephrine reuptake inhibitors (SNRIs), including SAVELLA, may cause sexual problems.
Symptoms in males may include

- Delayed ejaculation or inability to have an ejaculation
- Decreased sex drive
- Problems getting or keeping an erection

Symptoms in females may include

- Decreased sex drive
- Delayed orgasm or inability to have an orgasm

Talk to your healthcare provider if you develop any changes in your sexual function or if you have any questions or concerns about sexual problems during treatment with SAVELLA. There may be treatments your healthcare provider can suggest.
Do not stop SAVELLA without first talking to your healthcare provider. Stopping SAVELLA too quickly may cause symptoms, some serious, including:

- anxiety, irritability, or confusion
- feeling tired or problems sleeping
- headache, dizziness, seizures
- electric shock-like sensations, ringing in ears

What is SAVELLA?
SAVELLA is a prescription medicine used to manage fibromyalgia. It is important to talk with your healthcare provider about the risks of treating fibromyalgia and also the risks of not treating it. You should discuss all treatment choices with your healthcare provider.
It is not known if SAVELLA is safe and effective in children.
Who should not take SAVELLA?
Do not take SAVELLA if you:

- take a Monoamine Oxidase Inhibitor (MAOI). Ask your healthcare provider or pharmacist if you are not sure if you take an MAOI, including the antibiotic linezolid.
  - Do not take an MAOI within 5 days of stopping SAVELLA unless your healthcare provider tells you to.
  - Do not start SAVELLA if you stopped taking an MAOI in the last 14 days unless your healthcare provider tells you to.
  - People who take SAVELLA close in time to an MAOI may have serious or even life-threatening side effects. Get medical help right away if you have any of these symptoms:
    - high fever
    - uncontrolled muscle spasms
    - stiff muscles
    - rapid changes in heart rate or blood pressure
    - confusion
    - loss of consciousness (pass out)

What should I tell my healthcare provider before taking SAVELLA?
Before starting SAVELLA, tell your healthcare provider if you:

- have heart problems or high blood pressure
- have liver problems
- have kidney problems
- have or had seizures or convulsions
- have bipolar disorder or mania
- have low sodium levels in your blood
- have or had bleeding problems
- drink alcohol. Talk to your healthcare provider about how often and how much alcohol you drink.
- have any other medical conditions
- are pregnant or plan to become pregnant. It is not known if SAVELLA will harm your unborn baby.
- are breastfeeding or plan to breastfeed. SAVELLA can pass into your breast milk and may harm your baby. Talk to your healthcare provider about the best way to feed your baby while taking SAVELLA.

Tell your healthcare provider about all the medicines that you take, including prescription and over-the counter medicines, vitamins, and herbal supplements. SAVELLA and some medicines may interact with each other, may not work as well, or may cause serious side effects.
Especially tell your healthcare provider if you take:

- triptans used to treat migraine headache
- medicines used to treat mood, anxiety, psychotic or thought disorders, including tricyclics, lithium, buspirone, SSRIs, SNRIs or MAOIs
- tramadol, fentanyl, meperidine, methadone, or other opioids
- amphetamines
- the blood thinner warfarin (Coumadin, Jantoven)
- non-steroidal anti-inflammatory drug (NSAID) (like ibuprofen, naproxen or aspirin)
- over-the-counter supplements such as tryptophan or St. John’s Wort

Ask your healthcare provider for a list of these medicines if you are not sure.
Your healthcare provider or pharmacist can tell you if it is safe to take SAVELLA with your other medicines. Do not start or stop any medicine while taking SAVELLA without talking to your healthcare provider first.
How should I take SAVELLA?

- Take SAVELLA exactly as your healthcare provider tells you.
- Your healthcare provider will slowly increase your dose to find the dose that is right for you.
  - On the first day of treatment, you will take 1 dose of SAVELLA as prescribed.
  - After your first dose, your healthcare provider will tell you how much SAVELLA to take and when to take it, usually 2 times each day.
- You may take SAVELLA with or without food. Taking SAVELLA with food may help you tolerate it better.
- If you miss a dose, skip the missed dose and take the next dose at your regular time.
- Tell your healthcare provider if you feel that your condition is not improving during treatment with SAVELLA.
- If you take too much SAVELLA, call your healthcare provider or go to the nearest hospital emergency room right away.

What should I avoid while taking SAVELLA?

- Do not drive or operate machinery until you know how SAVELLA affects you. SAVELLA may make you less alert and affect your reaction time.

What are the possible side effects of SAVELLA?
SAVELLA may cause side effects, some serious, including:

- See “What is the most important information I should know about SAVELLA?”

The most common side effects of SAVELLA include:

• nausea

• vomiting

• headache

• irregular heartbeat (palpitations)

• constipation

• heart rate increased

• dizziness

• dry mouth

• trouble sleeping

• high blood pressure (hypertension)

• hot flush

• increased sweating

Tell your healthcare provider if you have any side effect that bothers you or that does not go away.
These are not all the possible side effects of SAVELLA. For more information, ask your healthcare provider or pharmacist.
Call your doctor for medical advice about side effects. You may report side effects to FDA at 1-800-FDA-1088.
How should I store SAVELLA?

- Store at room temperature between 68°F to 77°F (20°C to 25°C).

Keep SAVELLA and all medicines out of the reach of children.
General information about the safe and effective use of SAVELLA
Medicines are sometimes prescribed for purposes other than those listed in a Medication Guide. Do not use SAVELLA for a condition for which it was not prescribed. Do not give SAVELLA to other people, even if they have the same condition. It may harm them.
You may ask your healthcare provider or pharmacist for information about SAVELLA that is written for health professionals.
For more information call 1-800-678-1605 or go to www.savella.com.
What are the ingredients in SAVELLA?
Active ingredient: milnacipran hydrochloride
Inactive ingredients: dibasic calcium phosphate, povidone, carboxymethylcellulose calcium, colloidal silicon dioxide, magnesium stearate, and talc.
The film coat contains the inactive ingredients:
12.5 mg tablets: FD&C Blue #2 Aluminum Lake, polyvinyl alcohol, polyethylene glycol, talc, titanium dioxide
25 mg tablets: Polyvinyl alcohol, polyethylene glycol, talc, titanium dioxide
50 mg tablets: Polyvinyl alcohol, polyethylene glycol, talc, titanium dioxide
100 mg tablets: FD&C Red #40 Aluminum Lake, polyvinyl alcohol, polyethylene glycol, talc, titanium dioxide
This Medication Guide has been approved by the U.S. Food and Drug Administration.
Distributed by:
AbbVie Inc.
1 N Waukegan Rd.
North Chicago, IL 60064
Licensed from Pierre Fabre Medicament
© 2025 AbbVie. All rights reserved.
SAVELLA and its design are trademarks of Allergan Sales, LLC, an AbbVie company.

Distributed By:

Cardinal Health

Dublin, OH 43017

ER7800 Rev. D

20091024

Revised: September 2025

Package/Label Display Panel

Contains Approximately

1920 Tablets

SAVELLA®

(milnacipran HCl) Tablets

50 mg

Each tablet contains:

50 mg milnacipran HCl.

Dispense the Medication Guide to each

patient.

Rx Only

WARNING: Keep out of reach of

children.